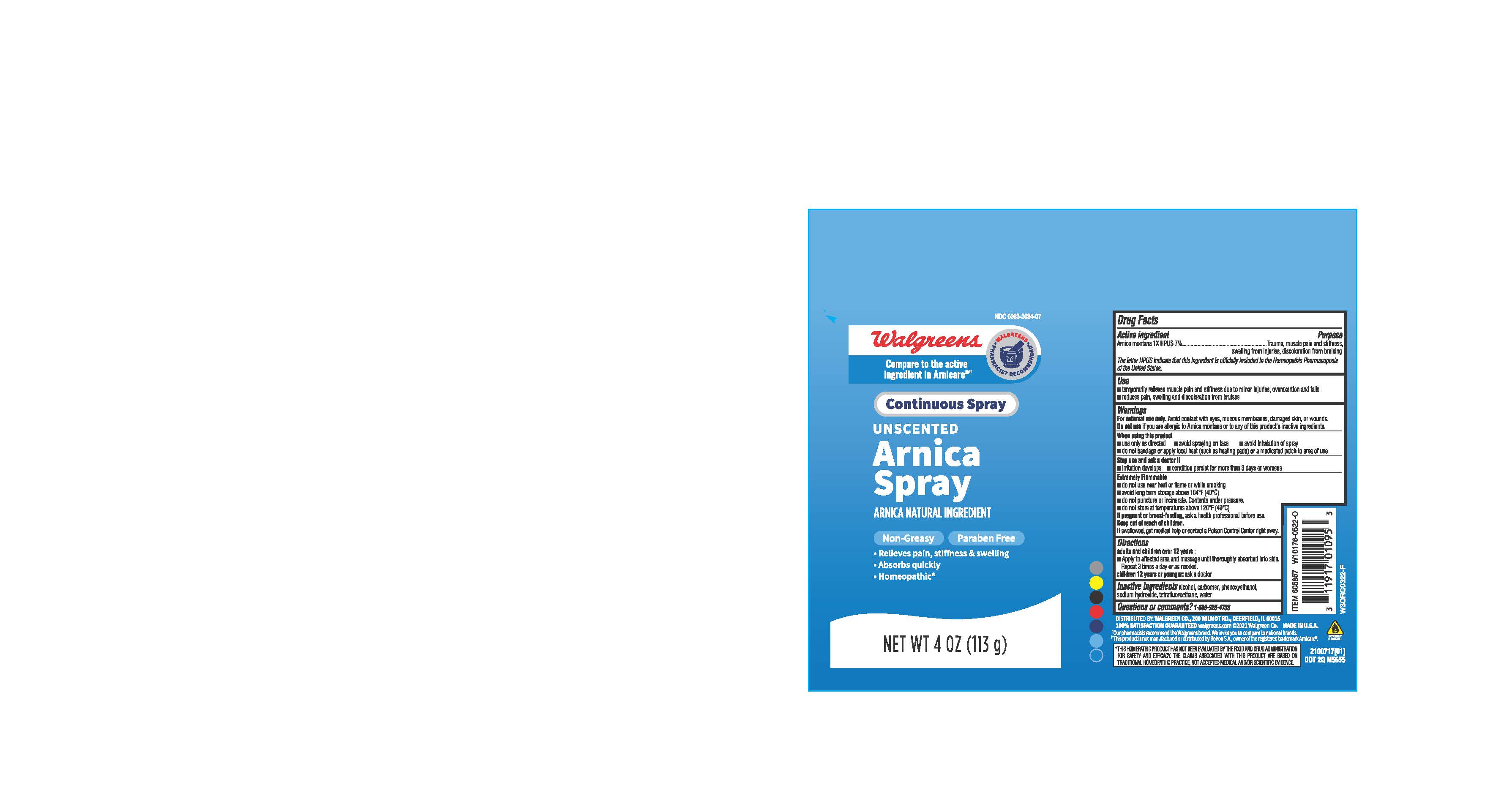 DRUG LABEL: Walgreens Arnica
NDC: 0363-3034 | Form: AEROSOL, SPRAY
Manufacturer: Walgreens
Category: homeopathic | Type: HUMAN OTC DRUG LABEL
Date: 20221130

ACTIVE INGREDIENTS: ARNICA MONTANA 1 [hp_X]/1 g
INACTIVE INGREDIENTS: ISOPROPYL ALCOHOL; SODIUM HYDROXIDE; NORFLURANE; WATER; CARBOMER 940; PHENOXYETHANOL

Walgreens Arnica Spray

ACTIVE INGREDIENT

Arnica montana 1 X HPUS 7%

PURPOSE

Trauma, muscle pain and stiffness, swelling from injuries, discoloration from bruising

INDICATIONS AND USAGE

Temporarily relieves muscle pain and stiffness due to minor injuries, overexertion and falls

reduces pain, swelling and discoloration from bruises.

WARNINGS

For external use only

Do not use if you are allergic to Arnica montana or to any of this product's inactive ingredients.

Extremely Flammable

do not use near heat or flame or while smoking

avoid long term storage above 104°F (40°C)

do not puncture or incinerate. Contents under pressure

do not store at temperatures above 120°F (49°C)

When using this product

Use only as directed

Avoid spraying on face

Avoid inhalation of spray

Do not bandage or apply local heat (such as heating pads) or a medicated patch to area of use

Stop use and ask a doctor if

irritation develops

condition persist for more than 3 days or worsens

PREGNANCY OR BREAST FEEDING

If pregnant or breast feeding, ask a health professional before use.

Keep out of reach of children.

If swallowed, get medical help or contact a poison Control Center right away.

Directions:

adults and children over 12 years:

Apply to affected area and massage until thoroughly absorbed into skin.

Repeat 3 times a day or as needed.

Children 12 years or younger: ask a doctor

INACTIVE INGREDIENT

Alcohol, Carbomer, phenoxyethanol, sodium hydroxide, tetrafluoroethene, water

Questions or comments ? 1-800-925-4733